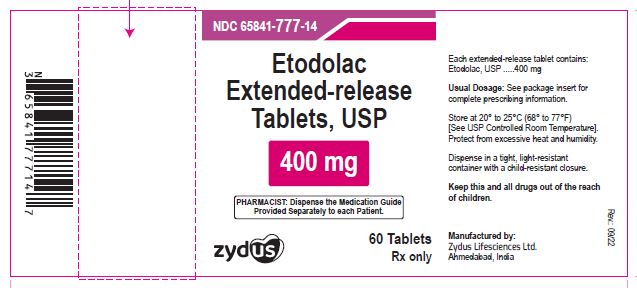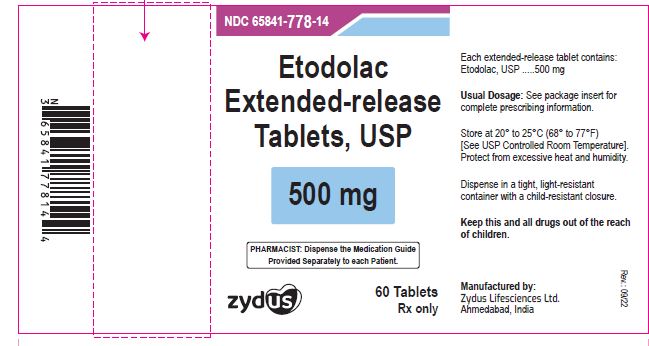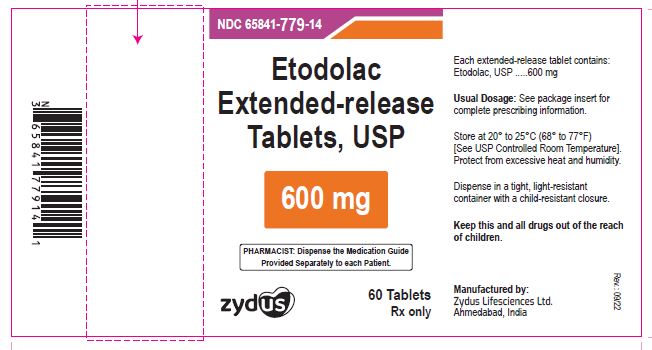 DRUG LABEL: Etodolac
NDC: 65841-777 | Form: TABLET, FILM COATED, EXTENDED RELEASE
Manufacturer: Zydus Lifesciences Limited
Category: prescription | Type: HUMAN PRESCRIPTION DRUG LABEL
Date: 20241128

ACTIVE INGREDIENTS: ETODOLAC 400 mg/1 1
INACTIVE INGREDIENTS: D&C YELLOW NO. 10; ETHYLCELLULOSE (100 MPA.S); FD&C RED NO. 40; FD&C YELLOW NO. 6; HYPROMELLOSES; LACTOSE MONOHYDRATE; MAGNESIUM STEARATE; POLYETHYLENE GLYCOL, UNSPECIFIED; TALC; TITANIUM DIOXIDE; TRIACETIN; SODIUM PHOSPHATE, DIBASIC, ANHYDROUS

Etodolac Extended-release Tablets, USP

PACKAGE LABEL.PRINCIPAL DISPLAY PANEL

NDC 65841-777-14 in bottle of 60 tablets

Etodolac Extended-release Tablets USP, 400 mg

Rx only

60 tablets

NDC 65841-778-14 in bottle of 60 tablets

Etodolac Extended-release Tablets USP, 500 mg

Rx only

60 tablets

NDC 65841-779-14 in bottle of 60 tablets

Etodolac Extended-release Tablets USP, 600 mg

Rx only

60 tablets